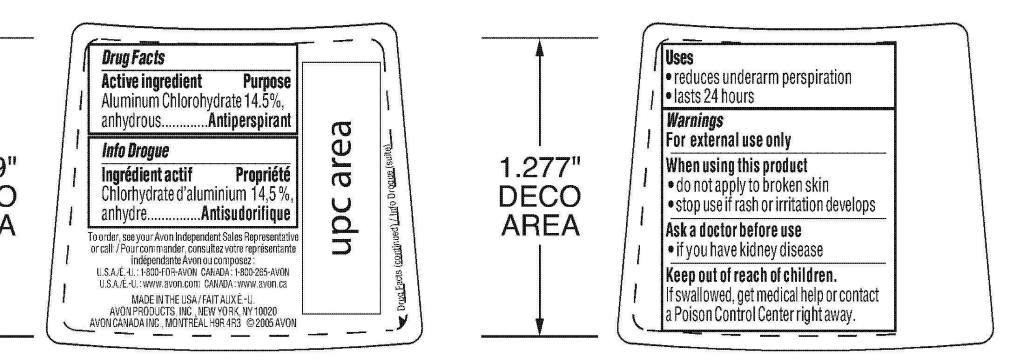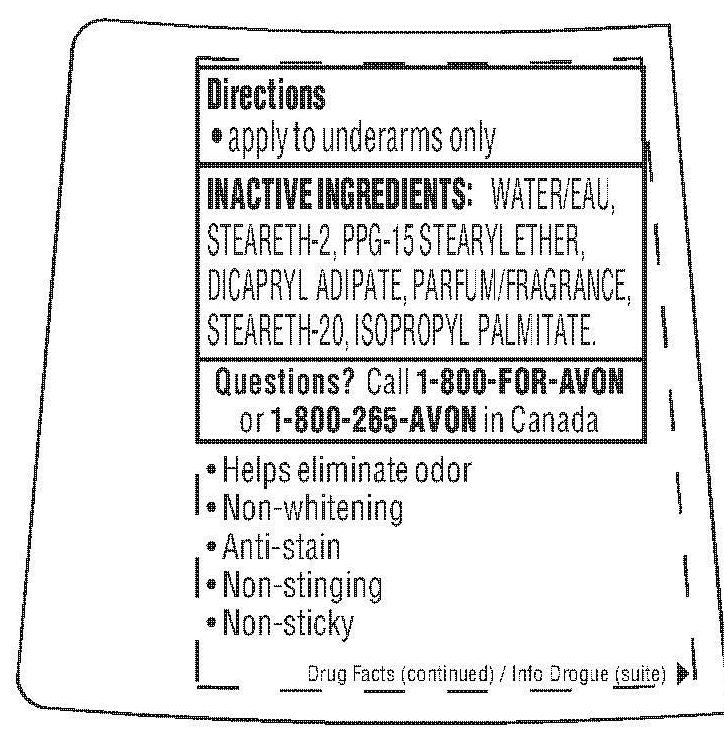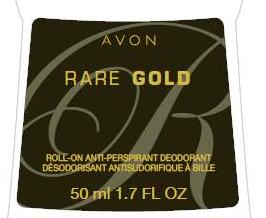 DRUG LABEL: Rare Gold
NDC: 10096-0269 | Form: GEL
Manufacturer: New Avon LLC
Category: otc | Type: HUMAN OTC DRUG LABEL
Date: 20190617

ACTIVE INGREDIENTS: ALUMINUM CHLOROHYDRATE 145 mg/1 mL
INACTIVE INGREDIENTS: WATER

Rare Gold ROD

Active ingredient
Aluminum Chlorohydrate
14.5%, anhydrous...........

Purpose
............. Antiperspirant

Uses
• reduces underarm perspiration
• lasts 24 hours

Warnings
For external use only

When using this product
• do not apply to broken skin
• stop use if rash or irritation develops

Ask a doctor before use
• if you have kidney disease

Keep out of reach of children.
If swallowed, get medical help or
contact a Poison Control Center
right away.

Directions
• apply to underarms only

INACTIVE INGREDIENTS :
WATER/EAU, STEARETH-2,
PPG-15 STEARYL ETHER,
DICAPRYL ADIPATE, PARFUM/
FRAGRANCE, STEARETH-20,
ISOPROPYL PALMITATE.

Questions? Call 1-800-FOR-AVON
or 1-800-265-AVON in Canada